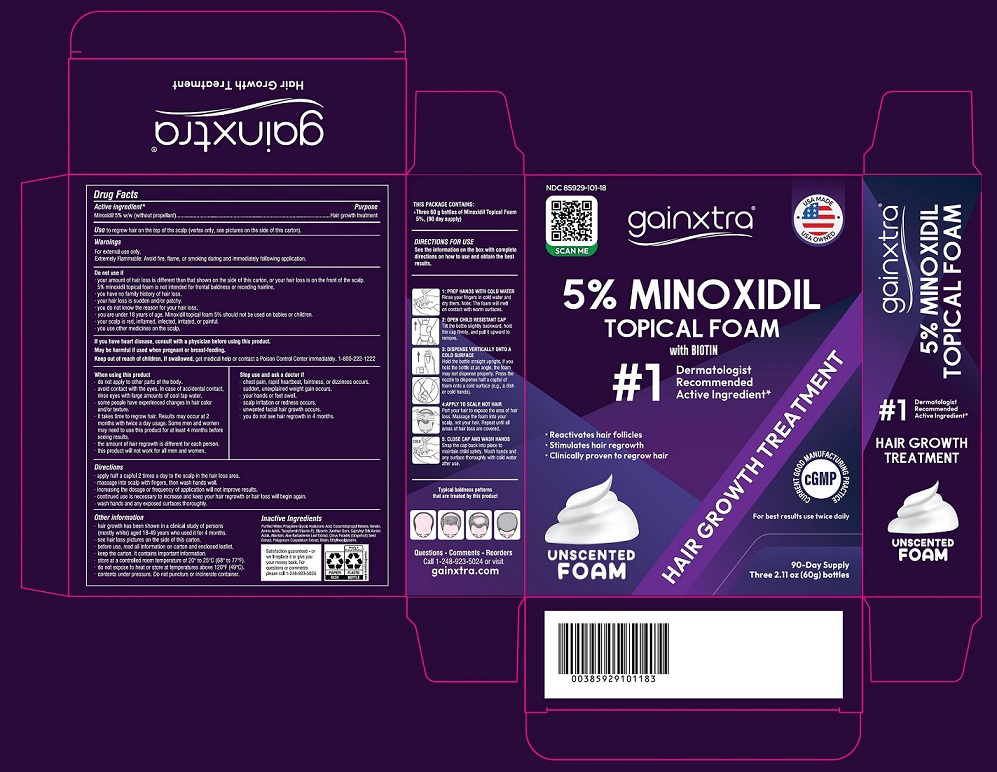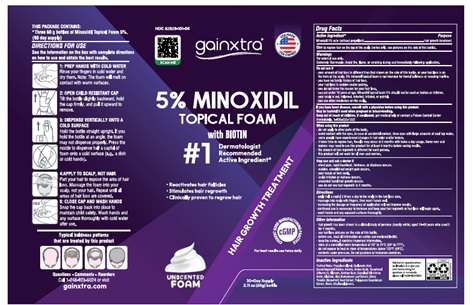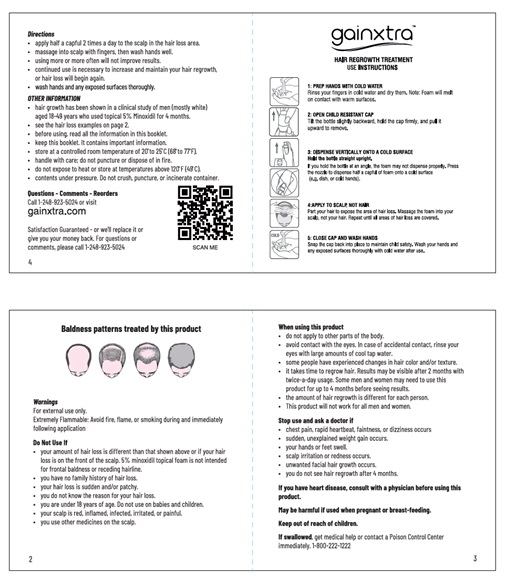 DRUG LABEL: Gainxtra Hair Regrowth Treatment for Men and Women Minoxidil 5% Form with Biotin
NDC: 85929-101 | Form: AEROSOL, FOAM
Manufacturer: GAINXTRA LLC
Category: otc | Type: HUMAN OTC DRUG LABEL
Date: 20251110

ACTIVE INGREDIENTS: MINOXIDIL 50 mg/1 g
INACTIVE INGREDIENTS: WATER; PROPYLENE GLYCOL; HYALURONIC ACID; COCAMIDOPROPYL BETAINE; HAIR KERATIN AMINO ACIDS; AMINO ACIDS, SOURCE UNSPECIFIED; TOCOPHEROL; GLYCERIN; XANTHAN GUM; ALLANTOIN; ALOE VERA LEAF; CITRUS PARADISI SEED; REYNOUTRIA JAPONICA WHOLE; BIOTIN; ETHYLHEXYLGLYCERIN

Gainxtra Hair Regrowth Treatment for Men and Women Minoxidil 5% Form with Biotin

DRUG FACTS

ACTIVE INGREDIENT

Minoxidil 5% w/w

(without propellant)

PURPOSE

Hair regrowth treatment for men and women

USE

To regrow hair the scalp

WARNINGS

For external use only.

Extremely Flammable: Avoid Fire, flame, or smoking during and immediately following application.

Do not use if:

- the amount of hair loss is different the amount that is shown on the carton or your hair loss is on the front of the scalp. 5% Minoxidil Form is not intended for frontal baldness of receding hairline.
- you have no family history of hair loss
- your hair is sudden and/or patchy
- you do not know the reason for your hair loss
- you are 18 years of age. Do not use on babies and children
- your scalp is red, inflamed, infected, irritated, or painful
- you use other medicines on the scalp

Ask a doctor before use if you have heart disease.

When using this product

- do not apply to other body parts
- avoid contact with the eyes. In case of accidental contact, rinse eyes with large amounts of cool tap water
- some people have experienced changes in hair color and/or texture
- it takes time to regrow hair. Some men and women may need to use this product for up to 4 months before seeing results
- the amount of hair regrowth is different for each person. This product will not work for all men and women

Stop use and ask a doctor if

- chest pain, rapid heartbeat, faintness, or dizziness occurs
- sudden, unexplained weight gain occurs
- your hands or feet swell
- scalp irritation or redness occurs
- unwanted facial hair growth occurs
- you do not see hair regrowth within 4 months

May be harmful if used when pregnant or breast-feeding. Keep out of reach of children.

If swallowed get medical help or contact a Poison Control Center right away. (1-800-222-1222)

Directions

- apply half a capful 2 times a day to the scalp in the hair loss area
- massage into scalp with fingers, then wash hands.
- using more or more often will not improve results.
- continued use is necessary to increase and maintain your hair regrowth or hair loss will begin again

Other information

- hair growth has been shown in a clinical study of men and women aged 18-49 years who used it for 4 months
- read all information and the enclosed leaflet before use
- store at this controlled room temperature 20° to 25°C (68° to 77°F)
- do not expose to hear or store in temperatures above 120°F (49°C)
- increasing the dose or frequency of use will not accelerate hair growth

Inactive ingredients

Purified water, Propylene Glycol, Hyaluronic Acid, Cocamidopropyl Betadine, Keratine, Amino Acids, Tocopherol (Vitamin E), Glycerin, Xanthan Gum, Capryloyl Silk Amino Acids, Allantoin, Aloe Barbadensis Leaf Extract, Citrus Paradisi (Grapefruit) Seed Extract, Polygonum Cuspidatum Extract, Biotin, Ethylhexylglycerin.

Questions?

Call(1-248-923-5024) or gainxtra.com

Manufactured for and distributed by:

Gainxtra LLC

3162 Martin Road

Commerce Township, MI 48390

PACKAGE LABEL

Save this leaflet for future reference.